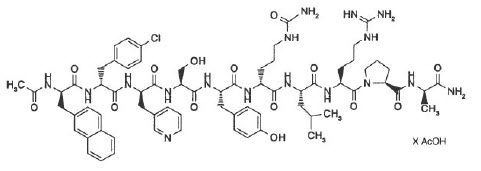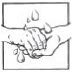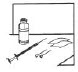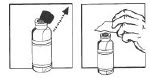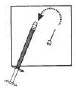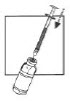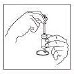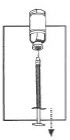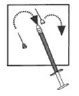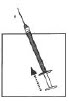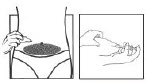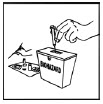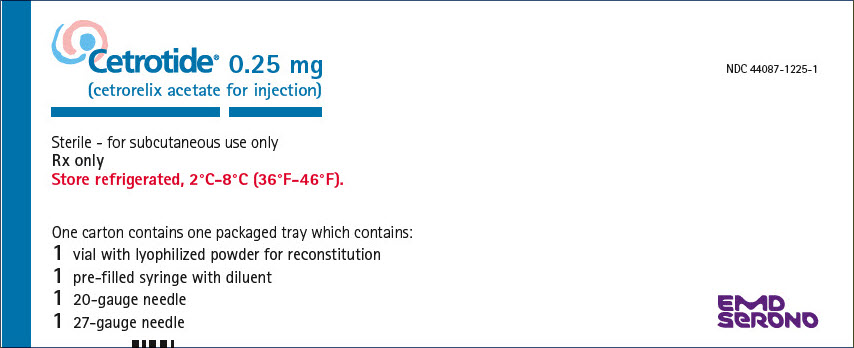 DRUG LABEL: Cetrotide
NDC: 44087-1225 | Form: KIT | Route: SUBCUTANEOUS
Manufacturer: EMD Serono, Inc.
Category: prescription | Type: HUMAN PRESCRIPTION DRUG LABEL
Date: 20250922

ACTIVE INGREDIENTS: CETRORELIX ACETATE 0.25 mg/1 mL
INACTIVE INGREDIENTS: MANNITOL 54.80 mg/1 mL; WATER 1 mL/1 mL

Cetrotide® 0.25 mg
(cetrorelix acetate for injection)

FOR SUBCUTANEOUS USE ONLY

DESCRIPTION

Cetrotide® (cetrorelix acetate for injection) is a synthetic decapeptide with gonadotropin-releasing hormone (GnRH) antagonistic activity. Cetrorelix acetate is an analog of native GnRH with substitutions of amino acids at positions 1, 2, 3, 6, and 10. The molecular formula is Acetyl-D-3-(2´-naphthyl)-alanine-D-4-chlorophenylalanine-D-3-(3´-pyridyl)-alanine-L-serine-L-tyrosine-D-citrulline-L-leucine-L-arginine-L-proline-D-alanine-amide, and the molecular weight is 1431.06, calculated as the anhydrous free base. The structural formula is as follows:

Cetrorelix acetate

(Ac-D-Nal1-D-Cpa2-D-Pal3-Ser4-Tyr5-D-Cit6-Leu7-Arg8-Pro9-D-Ala10-NH2)

Cetrotide® (cetrorelix acetate for injection) 0.25 mg is a sterile lyophilized powder intended for subcutaneous injection after reconstitution with Sterile Water for Injection, that comes supplied in a 1.0 mL pre-filled syringe. Each vial of Cetrotide® 0.25 mg contains 0.26-0.27 mg cetrorelix acetate, equivalent to 0.25 mg cetrorelix, and 54.80 mg mannitol.

CLINICAL PHARMACOLOGY

GnRH induces the production and release of luteinizing hormone (LH) and follicle stimulating hormone (FSH) from the gonadotrophic cells of the anterior pituitary. Due to a positive estradiol (E2) feedback at midcycle, GnRH liberation is enhanced resulting in an LH-surge. This LH-surge induces the ovulation of the dominant follicle, resumption of oocyte meiosis and subsequently luteinization as indicated by rising progesterone levels.

Cetrotide® competes with natural GnRH for binding to membrane receptors on pituitary cells and thus controls the release of LH and FSH in a dose-dependent manner. The onset of LH suppression is approximately one hour with the 3 mg dose and two hours with the 0.25 mg dose. This suppression is maintained by continuous treatment and there is a more pronounced effect on LH than on FSH. An initial release of endogenous gonadotropins has not been detected with Cetrotide®, which is consistent with an antagonist effect.

The effects of Cetrotide® on LH and FSH are reversible after discontinuation of treatment. In women, Cetrotide® delays the LH-surge, and consequently ovulation, in a dose-dependent fashion. FSH levels are not affected at the doses used during controlled ovarian stimulation. Following a single 3 mg dose of Cetrotide®, duration of action of at least 4 days has been established. A dose of Cetrotide® 0.25 mg every 24 hours has been shown to maintain the effect.

Pharmacokinetics

The pharmacokinetic parameters of single and multiple doses of Cetrotide® (cetrorelix acetate for injection) in adult healthy female subjects are summarized in Table 1.

Table 1: Pharmacokinetic parameters of Cetrotide® following 3 mg single or 0.25 mg single and multiple (daily for 14 days) subcutaneous (sc) administration.
 | Single dose 3 mg | Single dose 0.25 mg | Multiple dose 0.25 mg
No. of subjects | 12 | 12 | 12
tmax [median (min-max)] [h] | 1.5 (0.5-2) | 1.0 (0.5-1.5) | 1.0 (0.5-2)
t1/2 [h] | 62.8 (38.2-108) | 5.0 (2.4-48.8) | 20.6 (4.1-179.3)
Cmax [ng/ml] | 28.5 (22.5-36.2) | 4.97 (4.17-5.92) | 6.42 (5.18-7.96)
AUC [ng∙h/ml] | 536 (451-636) | 31.4 (23.4-42.0) | 44.5 (36.7-54.2)
CL [arithmetic mean,] [ml/min∙kg] | 1.28 [Based on iv administration (n=6, separate study 0013)]
Vz [l/kg] | 1.16
tmax Time to reach observed maximum plasma concentration
t1/2 Elimination half-life
Cmax Maximum plasma concentration; multiple dose Css, max
AUC Area under the curve; single dose AUC0-inf, multiple dose AUCt
CL Total plasma clearance
Vz Volume of distribution
Geometric mean (95% CIln),

Absorption

Cetrotide® is rapidly absorbed following subcutaneous injection, maximal plasma concentrations being achieved approximately one to two hours after administration. The mean absolute bioavailability of Cetrotide® following subcutaneous administration to healthy female subjects is 85%.

Distribution

The volume of distribution of Cetrotide® following a single intravenous dose of 3 mg is about 1 l/kg. In vitro protein binding to human plasma is 86%.

Cetrotide® concentrations in follicular fluid and plasma were similar on the day of oocyte pick-up in patients undergoing controlled ovarian stimulation. Following subcutaneous administration of Cetrotide® 0.25 mg and 3 mg, plasma concentrations of cetrorelix were below or in the range of the lower limit of quantitation on the day of oocyte pick-up and embryo transfer.

Metabolism

After subcutaneous administration of 10 mg Cetrotide® to females and males, Cetrotide® and small amounts of (1-9), (1-7), (1-6), and (1-4) peptides were found in bile samples over 24 hours.

In in vitro studies, Cetrotide® was stable against phase I- and phase II-metabolism. Cetrotide® was transformed by peptidases, and the (1-4) peptide was the predominant metabolite.

Excretion

Following subcutaneous administration of 10 mg cetrorelix to males and females, only unchanged cetrorelix was detected in urine. In 24 hours, cetrorelix and small amounts of the (1-9), (1-7), (1-6), and (1-4) peptides were found in bile samples. 2-4% of the dose was eliminated in the urine as unchanged cetrorelix, while 5-10% was eliminated as cetrorelix and the four metabolites in bile. Therefore, only 7-14% of the total dose was recovered as unchanged cetrorelix and metabolites in urine and bile up to 24 hours. The remaining portion of the dose may not have been recovered since bile and urine were not collected for a longer period of time.

Special Populations

Pharmacokinetic investigations have not been performed either in subjects with impaired renal or liver function, or in the elderly, or in children (see PRECAUTIONS).

Pharmacokinetic differences in different races have not been determined.

There is no evidence of differences in pharmacokinetic parameters for Cetrotide® between healthy subjects and patients undergoing controlled ovarian stimulation.

Drug-Drug Interactions

No formal drug-drug interaction studies have been performed with Cetrotide® (see PRECAUTIONS).

Clinical Studies

Seven hundred thirty two (732) patients were treated with Cetrotide® (cetrorelix acetate for injection) in five (two Phase 2 dose-finding and three Phase 3) clinical trials. The clinical trial population consisted of Caucasians (95.5%) and Black, Asian, Arabian and others (4.5%). Women were between 19 and 40 years of age (mean: 32). The studies excluded subjects with polycystic ovary syndrome (PCOS), subjects with low or no ovarian reserve, and subjects with stage III-IV endometriosis.

Two dose regimens were investigated in these clinical trials, either a single dose per treatment cycle or multiple dosing. In the Phase 2 studies, a single dose of 3 mg was established as the minimal effective dose for the inhibition of premature LH surges with a protection period of at least 4 days. When Cetrotide® is administered in a multidose regimen, 0.25 mg was established as the minimal effective dose. The extent and duration of LH-suppression is dose dependent.

In the Phase 3 program, efficacy of the single 3 mg dose regimen of Cetrotide® and the multiple 0.25 mg dose regimen of Cetrotide® was established separately in two adequate and well controlled clinical studies utilizing active comparators. A third non-comparative clinical study evaluated only the multiple 0.25 mg dose regimen of Cetrotide®. The ovarian stimulation treatment with recombinant FSH or human menopausal gonadotropin (hMG) was initiated on day 2 or 3 of a normal menstrual cycle. The dose of gonadotropins was administered according to the individual patient's disposition and response.

In the single dose regimen study, Cetrotide® 3 mg was administered on the day of controlled ovarian stimulation when adequate estradiol levels (400 pg/mL) were obtained, usually on day 7 (range day 5-12). If hCG was not given within 4 days of the 3 mg dose of Cetrotide®, then 0.25 mg of Cetrotide® was administered daily beginning 96 hours after the 3 mg injection until and including the day of hCG administration.

In the two multiple dose regimen studies, Cetrotide® 0.25 mg was started on day 5 or 6 of COS. Both gonadotropins and Cetrotide® were continued daily (multiple dose regimen) until the injection of human chorionic gonadotropin (hCG).

Oocyte pick-up (OPU) followed by in vitro fertilization (IVF) or intracytoplasmic sperm injection (ICSI) as well as embryo transfer (ET) were subsequently performed. The results for Cetrotide® are summarized below in Table 2.

Table 2: Results of Phase 3 Clinical Studies with Cetrotide® (cetrorelix acetate for injection) 3 mg in a single dose (sd) regimen and 0.25 mg in a multiple dose (md) regimen
Parameter | Cetrotide® 3 mg (sd, active comparator study) | Cetrotide® 0.25 mg (md, active comparator study) | Cetrotide® 0.25 mg (md, non-comparative study)
No. of subjects | 115 | 159 | 303
hCG administered [%] | 98.3 | 96.2 | 96.0
Oocyte pick-up [%] | 98.3 | 94.3 | 93.1
LH-surge [%] (LH ≥ 10 U/L and P [Progesterone] ≥ 1 ng/mL) [Following initiation of Cetrotide® therapy] | 0.0 | 1.9 | 1.0
Serum E2 [pg/ml] at day hCG [Morning values] , [Median with 5th – 95th percentiles] | 1125 (470-2952) | 1064 (341-2531) | 1185 (311-3676)
Serum LH [U/L] at day hCG, | 1.0 (0.5-2.5) | 1.5 (0.5-7.6) | 1.1 (0.5-3.5)
No. of follicles ≥ 11 mm at day hCG [Mean ± standard deviation] | 11.2±5.5 | 10.8±5.2 | 10.4±4.5
No. of oocytes: IVF ICSI | 9.2±5.2 10.0±4.2 | 7.6±4.3 10.1±5.6 | 8.5±5.1 9.3±5.9
Fertilization rate: IVF ICSI | 0.48±0.33 0.66±0.29 | 0.62±0.26 0.63±0.29 | 0.60±0.26 0.61±0.25
No. of embryos transferred | 2.6±0.9 | 2.1±0.6 | 2.7±1.0
Clinical pregnancy rate [%]
per attempt | 22.6 | 20.8 | 19.8
per subject with ET | 26.3 | 24.1 | 23.3

In addition to IVF and ICSI, one pregnancy was obtained after intrauterine insemination. In the five Phase 2 and Phase 3 clinical trials, 184 pregnancies have been reported out of a total of 732 patients (including 21 pregnancies following the replacement of frozen-thawed embryos).

In the 3 mg regimen, 9 patients received an additional dose of 0.25 mg of Cetrotide® and two other patients received two additional doses of 0.25 mg Cetrotide®. The median number of days of Cetrotide® multiple dose treatment was 5 (range 1-15) in both studies.

No drug related allergic reactions were reported from these clinical studies.

INDICATIONS AND USAGE

Cetrotide® (cetrorelix acetate for injection) is indicated for the inhibition of premature LH surges in women undergoing controlled ovarian stimulation.

CONTRAINDICATIONS

Cetrotide® (cetrorelix acetate for injection) is contraindicated under the following conditions:

1. Hypersensitivity to cetrorelix acetate, extrinsic peptide hormones or mannitol.
2. Known hypersensitivity to GnRH or any other GnRH analogs.
3. Known or suspected pregnancy, and lactation (see PRECAUTIONS).
4. Severe renal impairment

WARNINGS

Cetrotide® (cetrorelix acetate for injection) should be prescribed by physicians who are experienced in fertility treatment. Before starting treatment with Cetrotide®, pregnancy must be excluded (see CONTRAINDICATIONS and PRECAUTIONS).

PRECAUTIONS

General

Cases of hypersensitivity reactions, including anaphylactoid reactions with the first dose, have been reported during post-marketing surveillance (see ADVERSE REACTIONS). A severe anaphylactic reaction associated with cough, rash, and hypotension, was observed in one patient after seven months of treatment with Cetrotide® (10 mg/day) in a study for an indication unrelated to infertility.

Special care should be taken in women with signs and symptoms of active allergic conditions or known history of allergic predisposition. Treatment with Cetrotide® is not advised in women with severe allergic conditions.

Information for Patients

Prior to therapy with Cetrotide® (cetrorelix acetate for injection), patients should be informed of the duration of treatment and monitoring procedures that will be required. The risk of possible adverse reactions should be discussed (see ADVERSE REACTIONS). Cetrotide® should not be prescribed if a patient is pregnant.

If Cetrotide® is prescribed to patients for self-administration, information for proper use is given in the Patient Leaflet (see below).

Laboratory Tests

After the exclusion of preexisting conditions, enzyme elevations (ALT, AST, GGT, alkaline phosphatase) were found in 1-2% of patients receiving Cetrotide® during controlled ovarian stimulation. The elevations ranged up to three times the upper limit of normal. The clinical significance of these findings was not determined.

During stimulation with human menopausal gonadotropin, Cetrotide® had no notable effects on hormone levels aside from inhibition of LH surges.

Drug Interactions

No formal drug interaction studies have been performed with Cetrotide®.

Carcinogenesis, Mutagenesis, Impairment of Fertility

Long-term carcinogenicity studies in animals have not been performed with cetrorelix acetate. Cetrorelix acetate was not genotoxic in vitro (Ames test, HPRT test, chromosome aberration test) or in vivo (chromosome aberration test, mouse micronucleus test). Cetrorelix acetate induced polyploidy in CHL-Chinese hamster lung fibroblasts, but not in V79-Chinese hamster lung fibroblasts, cultured peripheral human lymphocytes or in an in vitro micronucleus test in the CHL-cell line. Treatment with 0.46 mg/kg cetrorelix acetate for 4 weeks resulted in complete infertility in female rats which was reversed 8 weeks after cessation of treatment.

Pregnancy

(see CONTRAINDICATIONS)

Cetrotide® is contraindicated in pregnant women.

When administered to rats for the first seven days of pregnancy, cetrorelix acetate did not affect the development of the implanted conceptus at doses up to 38 μg/kg (approximately 1 times the recommended human therapeutic dose based on body surface area). However, a dose of 139 μg/kg (approximately 4 times the human dose) resulted in a resorption rate and a postimplantation loss of 100%. When administered from day 6 to near term to pregnant rats and rabbits, very early resorptions and total implantation losses were seen in rats at doses from 4.6 μg/kg (0.2 times the human dose) and in rabbits at doses from 6.8 μg/kg (0.4 times the human dose). In animals that maintained their pregnancy, there was no increase in the incidence of fetal abnormalities.

The fetal resorption observed in animals is a logical consequence of the alteration in hormonal levels effected by the antigonadotrophic properties of Cetrotide®, which could result in fetal loss in humans as well. Therefore, this drug should not be used in pregnant women.

Nursing Mothers

It is not known whether Cetrotide® is excreted in human milk. Because many drugs are excreted in human milk, and because the effects of Cetrotide® on lactation and/or the breast-fed child have not been determined, Cetrotide® should not be used by nursing mothers.

Geriatric Use

Cetrotide® is not intended to be used in subjects aged 65 and over.

ADVERSE REACTIONS

The safety of Cetrotide® (cetrorelix acetate for injection) in 949 patients undergoing controlled ovarian stimulation in clinical studies was evaluated. Women were between 19 and 40 years of age (mean: 32). 94.0% of them were Caucasian. Cetrotide® was given in doses ranging from 0.1 mg to 5 mg as either a single or multiple dose.

Table 3 shows systemic adverse events, reported in clinical studies without regard to causality, from the beginning of Cetrotide® treatment until confirmation of pregnancy by ultrasound at an incidence ≥ 1% in Cetrotide® treated subjects undergoing COS.

Table 3: Adverse Events in ≥1%
(WHO preferred term) | Cetrotide® N=949 % (n)
Ovarian Hyperstimulation Syndrome [Intensity moderate or severe, or WHO Grade II or III, respectively] | 3.5 (33)
Nausea | 1.3 (12)
Headache | 1.1 (10)

Local site reactions (e.g. redness, erythema, bruising, itching, swelling, and pruritus) were reported. Usually, they were of a transient nature, mild intensity and short duration. During post-marketing surveillance, cases of mild to moderate Ovarian Hyperstimulation syndrome and cases of hypersensitivity reactions including anaphylactoid reactions have been reported.

Two stillbirths were reported in Phase 3 studies of Cetrotide®.

Congenital Anomalies

Clinical follow-up studies of 316 newborns of women administered Cetrotide® were reviewed. One infant of a set of twin neonates was found to have anencephaly at birth and died after four days. The other twin was normal. Developmental findings from ongoing baby follow-up included a child with a ventricular septal defect and another child with bilateral congenital glaucoma.

Four pregnancies that resulted in therapeutic abortion in Phase 2 and Phase 3 controlled ovarian stimulation studies had major anomalies (diaphragmatic hernia, trisomy 21, Klinefelter syndrome, polymalformation, and trisomy 18). In three of these four cases, intracytoplasmic sperm injection (ICSI) was the fertilization method employed; in the fourth case, in vitro fertilization (IVF) was the method employed.

The minor congenital anomalies reported include: supernumerary nipple, bilateral strabismus, imperforate hymen, congenital nevi, hemangiomata, and QT syndrome.

The causal relationship between the reported anomalies and Cetrotide® is unknown. Multiple factors, genetic and others (including, but not limited to ICSI, IVF, gonadotropins, and progesterone) make causal attribution difficult to study.

OVERDOSAGE

There have been no reports of overdosage with Cetrotide® 0.25 mg or 3 mg in humans. Single doses up to 120 mg Cetrotide® have been well tolerated in patients treated for other indications without signs of overdosage.

DOSAGE AND ADMINISTRATION

Ovarian stimulation therapy with gonadotropins (FSH, hMG) is started on cycle Day 2 or 3. The dose of gonadotropins should be adjusted according to individual response. Cetrotide® (cetrorelix acetate for injection) 0.25 mg may be administered subcutaneously once daily during the early- to mid-follicular phase.

Cetrotide® 0.25 mg is administered on either stimulation day 5 (morning or evening) or day 6 (morning) and continued daily until the day of hCG administration.

When assessment by ultrasound shows a sufficient number of follicles of adequate size, hCG is administered to induce ovulation and final maturation of the oocytes. No hCG should be administered if the ovaries show an excessive response to the treatment with gonadotropins to reduce the chance of developing ovarian hyperstimulation syndrome (OHSS).

Administration

Cetrotide® 0.25 mg can be administered by the patient herself after appropriate instructions by her doctor.

Directions for using Cetrotide® 0.25 mg with the enclosed needles and pre-filled syringe:

1. Wash hands thoroughly with soap and water.
2. Flip off the plastic cover of the vial and wipe the aluminum ring and the rubber stopper with an alcohol swab.
3. Twist the injection needle with the yellow mark (20 gauge) on the pre-filled syringe.
4. Push the needle through the center of the rubber stopper of the vial and slowly inject the solvent into the vial.
5. Leaving the syringe in the vial, gently swirl the vial until the solution is clear and without residues. Avoid forming bubbles.
6. Draw the total contents of the vial into the syringe. If necessary, invert the vial and pull back the needle as far as needed to withdraw the entire contents of the vial.
7. Replace the needle with the yellow mark by the injection needle with the grey mark (27 gauge).
8. Invert the syringe and push the plunger until all air bubbles have been expelled.
9. Choose an injection site in the lower abdominal area, preferably around, but staying at least one inch away from the navel. Choose a different injection site each day to minimize local irritation. Use a second alcohol swab to clean the skin at the injection site and allow alcohol to dry. Gently pinch up the skin surrounding the site of injection.
10. Inject the prescribed dose as directed by your doctor, nurse or pharmacist.
11. Use the syringe and needles only once. Dispose of the syringe and needles properly after use. If available, use a medical waste container for disposal.

HOW SUPPLIED

Cetrotide® (cetrorelix acetate for injection) 0.25 mg is available in a carton of one packaged tray (NDC 44087-1225-1).

Each packaged tray contains: one glass vial containing 0.26 - 0.27 mg cetrorelix acetate (corresponding to 0.25 mg cetrorelix), one pre-filled glass syringe with 1 mL of Sterile Water for Injection, one 20 gauge needle (yellow) and one 27 gauge needle (grey).

Storage

Store Cetrotide® 0.25 mg refrigerated, 2ºC - 8ºC (36ºF - 46ºF). Store the packaged tray in the outer carton in order to protect from light.

Rx only

Manufactured for:

EMD Serono, Inc, Boston, MA 02210, USA

July 2025

Patient Leaflet

Cetrotide® 0.25 mg

Active ingredient: cetrorelix acetate

Summary

Cetrotide® blocks the effects of a natural hormone, called gonadotropin-releasing hormone (GnRH). GnRH controls the secretion of another hormone, called luteinizing hormone (LH), which induces ovulation during the menstrual cycle. During hormone treatment for ovarian stimulation, premature ovulation may lead to eggs that are not suitable for fertilization. Cetrotide® blocks such undesirable premature ovulation.

Uses

Cetrotide® is used to prevent premature ovulation during controlled ovarian stimulation.

General Cautions

Do not use Cetrotide® if you

- have kidney disease
- are allergic to cetrorelix acetate, mannitol or exogenous peptide hormones (medicines similar to Cetrotide®) or
- are pregnant, or think that you might be pregnant, or if you are breast-feeding.

Consult your doctor before taking Cetrotide® if you have had severe allergic reactions.

Proper Use

Ovarian stimulation therapy is started on cycle Day 2 or 3. Cetrotide® 0.25 mg is injected under the skin once daily, as directed by your physician. When an ultrasound examination shows that you are ready, another drug (hCG) is injected to induce ovulation.

How should you use Cetrotide®?

You may self-inject Cetrotide® after special instruction from your doctor.

To fully benefit from Cetrotide®, please read carefully and follow the instructions given below, unless your doctor advises you otherwise.

Cetrotide® is for injection under the skin of the lower abdominal area, preferably around, but staying at least one inch away from the belly button. Choose a different injection site each day to minimize local irritation.

Dissolve Cetrotide® powder only with the water contained in the pre-filled syringe. Do not use a Cetrotide® solution if it contains particles or if it is not clear.

Before you inject Cetrotide® yourself, please read the following instructions carefully:

Directions for using Cetrotide® 0.25 mg with the enclosed needles and pre-filled syringe:

1. | Wash your hands thoroughly with soap and water.
2. | On a clean flat surface, lay out everything you need (one vial of powder, one pre-filled syringe, one injection needle with a yellow mark, and one injection needle with a grey mark).
3. | Flip off the plastic cover of the vial. Wipe the aluminum ring and the rubber stopper with an alcohol swab.
4. | Take the injection needle with the yellow mark and remove the wrapping. Take the pre-filled syringe and remove the cover. Twist the needle on the syringe and remove the cover of the needle.
5. | Push the needle through the center of the rubber stopper of the vial. Inject the water into the vial by slowly pushing down on the plunger of the syringe.
6. | Leave the syringe in the vial. While carefully holding the syringe and vial, swirl gently to mix the powder and water together. When it is mixed, it will look clear and have no particles in it. Do not shake or you will create bubbles in your medicine.
7. | Draw the total contents of the vial into the syringe. If liquid is left in the vial, invert the vial, pull back the needle until the opening of the needle is just inside the stopper. If you look from the side through the gap in the stopper, you can control the movement of the needle and the liquid. It is important to withdraw the entire contents of the vial.
8. | Detach the syringe from the needle and lay down the syringe. Take the injection needle with the grey mark and remove its wrapping. Twist the needle on the syringe and remove the cover of the needle.
9. | Invert the syringe and push the plunger until all air bubbles have been pushed out. Do not touch the needle or allow the needle to touch any surface.
10. | Choose an injection site in the lower abdominal area, preferably around, but at least one inch away from the belly button. Choose a different injection site each day to minimize local irritation. Take a second alcohol swab and clean the skin at the injection site and allow alcohol to dry. Inject the prescribed dose as directed by your doctor, nurse or pharmacist.
11. | Use the syringe and needles only once. Dispose of the syringe and needles immediately after use (put the covers on the needles to avoid injury). A medical waste container should be used for disposal.

SPECIAL ADVICE

What do you do if you have used too much Cetrotide®?

Contact your doctor in case of overdosage immediately to check whether an adjustment of the further ovarian stimulation procedure is required.

Possible Side Effects

Mild and short lasting reactions may occur at the injection site like reddening, itching, and swelling. Nausea and headache have also been reported.

Call your doctor if you have any side effect not mentioned in this leaflet or if you are unsure about the effect of this medicine.

Storage

How is Cetrotide® to be stored?

Store Cetrotide® in a cool dry place protected from excess moisture and heat.

Store Cetrotide® 0.25 mg in the refrigerator at 2°C - 8°C (36°F - 46°F). Keep the packaged tray in the outer carton in order to protect it from light.

How long may Cetrotide® be stored?

Do not use the Cetrotide® powder or the pre-filled syringe after the expiration date, which is printed on the labels and on the carton and dispose of the vial and the syringe properly.

How long can you keep Cetrotide® after preparation of the solution?

The solution should be used immediately after preparation.

Store the medicine out of the reach of children.

If you suspect that you may have taken more than the prescribed dose of this medicine, contact your doctor immediately. This medicine was prescribed for your particular condition. Do not use it for another condition or give the drug to others.

This leaflet provides a summary of the information about Cetrotide®. Medicines are sometimes prescribed for uses other than those listed in the Leaflet. If you have any questions or concerns, or want more information about Cetrotide®, contact your doctor or pharmacist.

This Leaflet has been approved by the U.S. Food and Drug Administration.

July 2025

PRINCIPAL DISPLAY PANEL - Kit Carton

Cetrotide® 0.25 mg
(cetrorelix acetate for injection)

NDC 44087-1225-1

Sterile - for subcutaneous use only
Rx only
Store refrigerated, 2°C-8°C (36°F-46°F).

One carton contains one packaged tray which contains:
1 vial with lyophilized powder for reconstitution
1 pre-filled syringe with diluent
1 20-gauge needle
1 27-gauge needle

EMD
SERONO